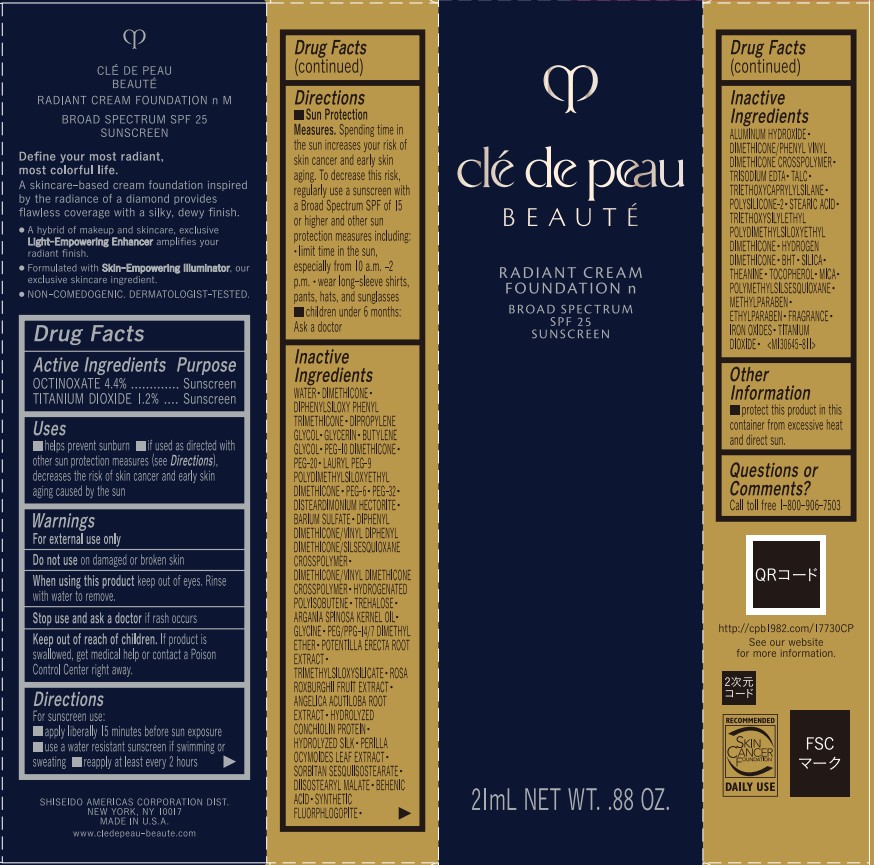 DRUG LABEL: cle de peau BEAUTE RADIANT FOUNDATION N M
NDC: 58411-976 | Form: CREAM
Manufacturer: Shiseido Americas Corporation
Category: otc | Type: HUMAN OTC DRUG LABEL
Date: 20260225

ACTIVE INGREDIENTS: OCTINOXATE 1.06 g/21 mL; TITANIUM DIOXIDE 0.29 g/21 mL
INACTIVE INGREDIENTS: WATER; DIMETHICONE; DIPHENYLSILOXY PHENYL TRIMETHICONE; DIPROPYLENE GLYCOL; GLYCERIN; BUTYLENE GLYCOL; PEG-10 DIMETHICONE (200 CST); PEG-20; LAURYL PEG-9 POLYDIMETHYLSILOXYETHYL DIMETHICONE; PEG-6; PEG-32; DISTEARDIMONIUM HECTORITE; BARIUM SULFATE; DIMETHICONE/VINYL DIMETHICONE CROSSPOLYMER (SOFT PARTICLE); HYDROGENATED POLYISOBUTENE (1300 MW); TREHALOSE; ARGANIA SPINOSA KERNEL OIL; GLYCINE; PEG/PPG-14/7 DIMETHYL ETHER; POTENTILLA ERECTA ROOT; TRIMETHYLSILOXYSILICATE (M/Q 0.6-0.8); ROSA ROXBURGHII FRUIT; ANGELICA ACUTILOBA ROOT; PERILLA OCYMOIDES SEED OIL; SORBITAN SESQUIISOSTEARATE; DIISOSTEARYL MALATE; BEHENIC ACID; ALUMINUM HYDROXIDE; DIMETHICONE/PHENYL VINYL DIMETHICONE CROSSPOLYMER; TRISODIUM EDTA; TALC; TRIETHOXYCAPRYLYLSILANE; STEARIC ACID; HYDROGEN DIMETHICONE (13 CST); BUTYLATED HYDROXYTOLUENE; SILICA; THEANINE; TOCOPHEROL; MICA; POLYMETHYLSILSESQUIOXANE (11 MICRONS); METHYLPARABEN; FERRIC OXIDE RED

cle de peau BEAUTE RADIANT FOUNDATION N M

Drug Facts

Active Ingredients | Purpose
Octinoxate 4.4% | Sunscreen
Titanium Dioxide 1.2% | Sunscreen

Uses

- helps prevent sunburn
- if used as directed with other sun protection measures (see Directions) decreases the risk of skin cancer and early skin aging caused by the sun

Warnings

For external use only

Do not use on damaged or broken skin

When using this product keep out of eyes. Rinse with water to remove.

Stop use and ask a doctor if rash occurs

Keep out of reach of children.If product is swallowed, get medical help or contact a Poison Control Center right away.

Directions

For sunscreen use:

- apply liberally 15 minutes before sun exposure
- use a water resistant sunscreen if swimming or sweating.
- reapply at least every 2 hours.
- Sun Protection Measures. Spending time in the sum increases your risk of skin cancer and early skin aging. To decrease this risk, regularly use a sunscreen with a Broad Spectrum SPF of 15 or higher and other sun protection measures including:

• limit time in the sun, especially from 10 a.m. - 2 p.m.

• wear long-sleeve shirts, pants, hats, and sunglasses

- children under 6 months: Ask a doctor

INACTIVE INGREDIENT

WATER･DIMETHICONE･DIPHENYLSILOXY PHENYL TRIMETHICONE･DIPROPYLENE GLYCOL･GLYCERIN･BUTYLENE GLYCOL･PEG-10 DIMETHICONE･PEG-20･LAURYL PEG-9 POLYDIMETHYLSILOXYETHYL DIMETHICONE･PEG-6･PEG-32･DISTEARDIMONIUM HECTORITE･BARIUM SULFATE･DIPHENYL DIMETHICONE/VINYL DIPHENYL DIMETHICONE/SILSESQUIOXANE CROSSPOLYMER･DIMETHICONE/VINYL DIMETHICONE CROSSPOLYMER･HYDROGENATED POLYISOBUTENE･TREHALOSE･ARGANIA SPINOSA KERNEL OIL･GLYCINE･PEG/PPG-14/7 DIMETHYL ETHER･POTENTILLA ERECTA ROOT EXTRACT･TRIMETHYLSILOXYSILICATE･ROSA ROXBURGHII FRUIT EXTRACT･ANGELICA ACUTILOBA ROOT EXTRACT･HYDROLYZED CONCHIOLIN PROTEIN･HYDROLYZED SILK･PERILLA OCYMOIDES LEAF EXTRACT･SORBITAN SESQUIISOSTEARATE･DIISOSTEARYL MALATE･BEHENIC ACID･SYNTHETIC FLUORPHLOGOPITE･ALUMINUM HYDROXIDE･DIMETHICONE/PHENYL VINYL DIMETHICONE CROSSPOLYMER･TRISODIUM EDTA･TALC･TRIETHOXYCAPRYLYLSILANE･POLYSILICONE-2･STEARIC ACID･TRIETHOXYSILYLETHYL POLYDIMETHYLSILOXYETHYL DIMETHICONE･HYDROGEN DIMETHICONE･BHT･SILICA･THEANINE･TOCOPHEROL･MICA･POLYMETHYLSILSESQUIOXANE･METHYLPARABEN･ETHYLPARABEN･FRAGRANCE･IRON OXIDES･TITANIUM DIOXIDE･

Other information

- protect this product in this container from excessive heat and direct sun.

Questions or Comments?

Call toll free 1-800-906-7503

PRINCIPAL DISPLAY PANEL - 21mL Tube Carton - I10

clé de peau

BEAUTÉ

RADIANT CREAM

FOUNDATION n

BROAD SPECTRUM

SPF 25

SUNSCREEN

21mL NET WT. .88 OZ.

PRINCIPAL DISPLAY PANEL - 21mL Tube Carton - B10

clé de peau

BEAUTÉ

RADIANT CREAM

FOUNDATION n

BROAD SPECTRUM

SPF 25

SUNSCREEN

21mL NET WT. .88 OZ.

PRINCIPAL DISPLAY PANEL - 21mL Tube Carton - B20

clé de peau

BEAUTÉ

RADIANT CREAM

FOUNDATION n

BROAD SPECTRUM

SPF 25

SUNSCREEN

21mL NET WT. .88 OZ.

PRINCIPAL DISPLAY PANEL - 21mL Tube Carton - B30

clé de peau

BEAUTÉ

RADIANT CREAM

FOUNDATION n

BROAD SPECTRUM

SPF 25

SUNSCREEN

21mL NET WT. .88 OZ.

PRINCIPAL DISPLAY PANEL - 21mL Tube Carton - B40

clé de peau

BEAUTÉ

RADIANT CREAM

FOUNDATION n

BROAD SPECTRUM

SPF 25

SUNSCREEN

21mL NET WT. .88 OZ.

PRINCIPAL DISPLAY PANEL - 21mL Tube Carton - B50

clé de peau

BEAUTÉ

RADIANT CREAM

FOUNDATION n

BROAD SPECTRUM

SPF 25

SUNSCREEN

21mL NET WT. .88 OZ.

PRINCIPAL DISPLAY PANEL - 21mL Tube Carton - B60

clé de peau

BEAUTÉ

RADIANT CREAM

FOUNDATION n

BROAD SPECTRUM

SPF 25

SUNSCREEN

21mL NET WT. .88 OZ.

PRINCIPAL DISPLAY PANEL - 21mL Tube Carton - B70

clé de peau

BEAUTÉ

RADIANT CREAM

FOUNDATION n

BROAD SPECTRUM

SPF 25

SUNSCREEN

21mL NET WT. .88 OZ.

PRINCIPAL DISPLAY PANEL - 21mL Tube Carton - B80

clé de peau

BEAUTÉ

RADIANT CREAM

FOUNDATION n

BROAD SPECTRUM

SPF 25

SUNSCREEN

21mL NET WT. .88 OZ.

PRINCIPAL DISPLAY PANEL - 21mL Tube Carton - B90

clé de peau

BEAUTÉ

RADIANT CREAM

FOUNDATION n

BROAD SPECTRUM

SPF 25

SUNSCREEN

21mL NET WT. .88 OZ.

PRINCIPAL DISPLAY PANEL - 21mL Tube Carton - B100

clé de peau

BEAUTÉ

RADIANT CREAM

FOUNDATION n

BROAD SPECTRUM

SPF 25

SUNSCREEN

21mL NET WT. .88 OZ.

PRINCIPAL DISPLAY PANEL - 21mL Tube Carton - BF10

clé de peau

BEAUTÉ

RADIANT CREAM

FOUNDATION n

BROAD SPECTRUM

SPF 25

SUNSCREEN

21mL NET WT. .88 OZ.

PRINCIPAL DISPLAY PANEL - 21mL Tube Carton - BF50

clé de peau

BEAUTÉ

RADIANT CREAM

FOUNDATION n

BROAD SPECTRUM

SPF 25

SUNSCREEN

21mL NET WT. .88 OZ.

PRINCIPAL DISPLAY PANEL - 21mL Tube Carton - BF60

clé de peau

BEAUTÉ

RADIANT CREAM

FOUNDATION n

BROAD SPECTRUM

SPF 25

SUNSCREEN

21mL NET WT. .88 OZ.

PRINCIPAL DISPLAY PANEL - 21mL Tube Carton - O10

clé de peau

BEAUTÉ

RADIANT CREAM

FOUNDATION n

BROAD SPECTRUM

SPF 25

SUNSCREEN

21mL NET WT. .88 OZ.

PRINCIPAL DISPLAY PANEL - 21mL Tube Carton - O20

clé de peau

BEAUTÉ

RADIANT CREAM

FOUNDATION n

BROAD SPECTRUM

SPF 25

SUNSCREEN

21mL NET WT. .88 OZ.

PRINCIPAL DISPLAY PANEL - 21mL Tube Carton - O30

clé de peau

BEAUTÉ

RADIANT CREAM

FOUNDATION n

BROAD SPECTRUM

SPF 25

SUNSCREEN

21mL NET WT. .88 OZ.

PRINCIPAL DISPLAY PANEL - 21mL Tube Carton - O40

clé de peau

BEAUTÉ

RADIANT CREAM

FOUNDATION n

BROAD SPECTRUM

SPF 25

SUNSCREEN

21mL NET WT. .88 OZ.

PRINCIPAL DISPLAY PANEL - 21mL Tube Carton - O50

clé de peau

BEAUTÉ

RADIANT CREAM

FOUNDATION n

BROAD SPECTRUM

SPF 25

SUNSCREEN

21mL NET WT. .88 OZ.

PRINCIPAL DISPLAY PANEL - 21mL Tube Carton - O60

clé de peau

BEAUTÉ

RADIANT CREAM

FOUNDATION n

BROAD SPECTRUM

SPF 25

SUNSCREEN

21mL NET WT. .88 OZ.

PRINCIPAL DISPLAY PANEL - 21mL Tube Carton - O70

clé de peau

BEAUTÉ

RADIANT CREAM

FOUNDATION n

BROAD SPECTRUM

SPF 25

SUNSCREEN

21mL NET WT. .88 OZ.

PRINCIPAL DISPLAY PANEL - 21mL Tube Carton - O80

clé de peau

BEAUTÉ

RADIANT CREAM

FOUNDATION n

BROAD SPECTRUM

SPF 25

SUNSCREEN

21mL NET WT. .88 OZ.

PRINCIPAL DISPLAY PANEL - 21mL Tube Carton - O90

clé de peau

BEAUTÉ

RADIANT CREAM

FOUNDATION n

BROAD SPECTRUM

SPF 25

SUNSCREEN

21mL NET WT. .88 OZ.

PRINCIPAL DISPLAY PANEL - 21mL Tube Carton - O100

clé de peau

BEAUTÉ

RADIANT CREAM

FOUNDATION n

BROAD SPECTRUM

SPF 25

SUNSCREEN

21mL NET WT. .88 OZ.